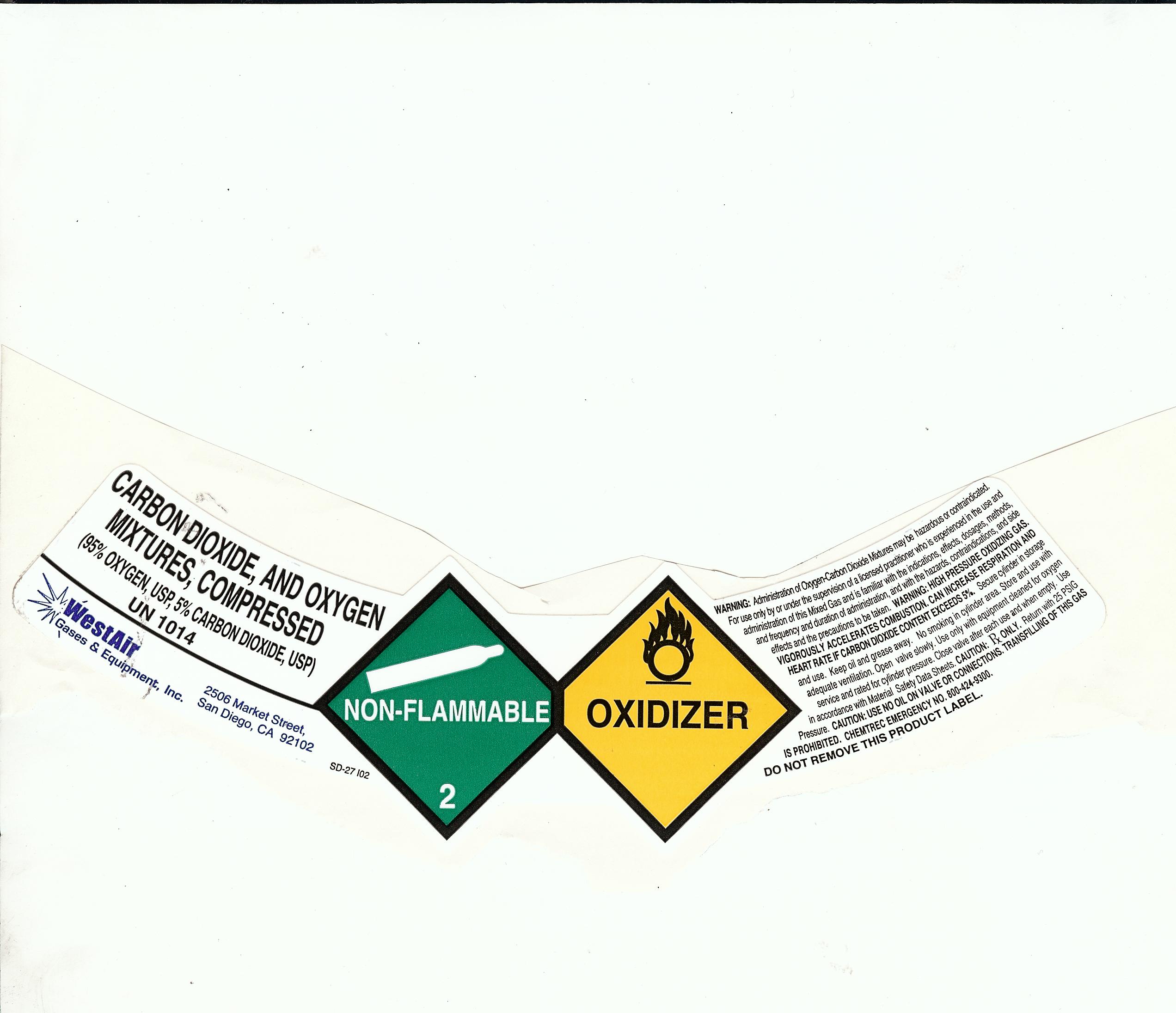 DRUG LABEL: Carbogen
NDC: 53440-006 | Form: GAS
Manufacturer: WestAir Gases and Equipment, Inc.
Category: prescription | Type: HUMAN PRESCRIPTION DRUG LABEL
Date: 20100203

ACTIVE INGREDIENTS: Carbon Dioxide 5 mL/1 L; Oxygen 95 mL/1 L

Carbogen

PACKAGE LABEL

CARBON DIOXIDE AND OXYGEN

MIXTURES, COMPRESSED

(95 PERCENT OXYGEN USP; 5 PERCENT CARBON DIOXIDE USP)

UN 1014

WestAir 2506 Market Street

Gases and Equipment, Inc. San Diego, Ca. 92102

NON-FLAMMABLE

2

OXIDIZER

WARNING: Administration of Oxygen-Carbon Dioxide Mixtures may be hazardous or contraindicated.

For use only by or under the supervision of a licensed practitioner who is experienced in the use and

administration of this Mixed Gas and is familiar with the indications, effects, dosages, methods,

and frequency and duration of administration, and with the hazards, contraindications, and side

effects and the precautions to be taken. WARNING: HIGH PRESSURE OXIDIZING GAS.

VIGOROUSLY ACCELERATES COMBUSTION. CAN INCREASE RESPIRATION AND

HEART RATE IF CARBON DIOXIDE CONTENT EXCEEDS 5 PERCENT. Secure cylinder in storage

and use. Keep oil and grease away. No smoking in cylinder area. Store and use with

adequate ventilation. Open valve slowly. use only equipment cleaned for oxygen

service and rated for cylinder pressure. Close valve after each use and when empty. Use

in accordance with Material Safety Datga Sheets. CAUTION: Rx ONLY. Return with 25 PSIG

Pressure. CAUTION: USE NO OIL ON VALVE OR CONNECTION. TRANSFILLING OF THIS GAS

IS PROHIBITED. CHEMTREC EMERGENCY NO. 800-424-9300

DO NOT REMOVE THIS PRODUCT LABEL